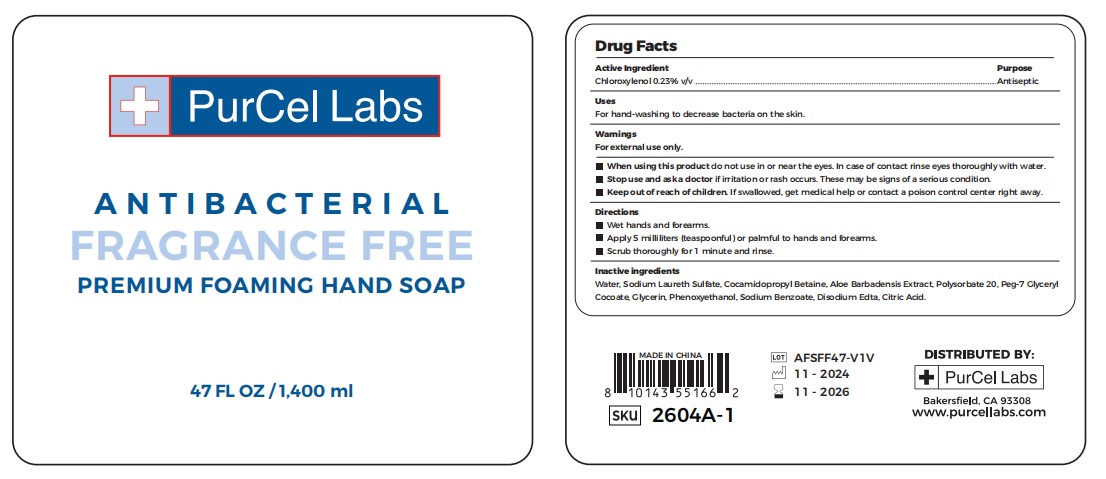 DRUG LABEL: Antibacterial wash hands foam
NDC: 83584-224 | Form: SOAP
Manufacturer: PurCel Labs LLC
Category: otc | Type: HUMAN OTC DRUG LABEL
Date: 20250112

ACTIVE INGREDIENTS: CHLOROXYLENOL 0.23 g/100 mL
INACTIVE INGREDIENTS: SODIUM LAURETH SULFATE; COCAMIDOPROPYL BETAINE; PHENOXYETHANOL; SODIUM BENZOATE; ALOE VERA LEAF; POLYSORBATE 20; GLYCERIN; WATER; PEG-7 GLYCERYL COCOATE; EDETATE DISODIUM; CITRIC ACID

Fragrance Free Foam 83584-224

Active Ingredient

Chloroxylenol 0.23% v/v

Purpose

Antiseptic

Uses

For hand-washing to decrease bacteria on the skin.

Warnings

For external use only.

When using this product do not use in or near the eyes. In case of contact rinse eyes thoroughly with water.

Stop use and ask a doctor if irritation or rash occurs. These may be signs of a serious condition.

Keep out of reach of children. If swallowed, get medical help or contact a poison control center right away.

Directions

Wet hands and forearms.
Apply 5 milliliters (teaspoonful) or palmful to hands and forearms.
Scrub thoroughly for 1 minute and rinse.

Inactive ingredients

Water, Sodium Laureth Sulfate, Cocamidopropyl Betaine, Aloe Barbadensis Extract, Polysorbate 20, Peg-7 Glyceryl
Cocoate, Glycerin, Phenoxyethanol, Sodium Benzoate, Disodium Edta, Citric Acid.